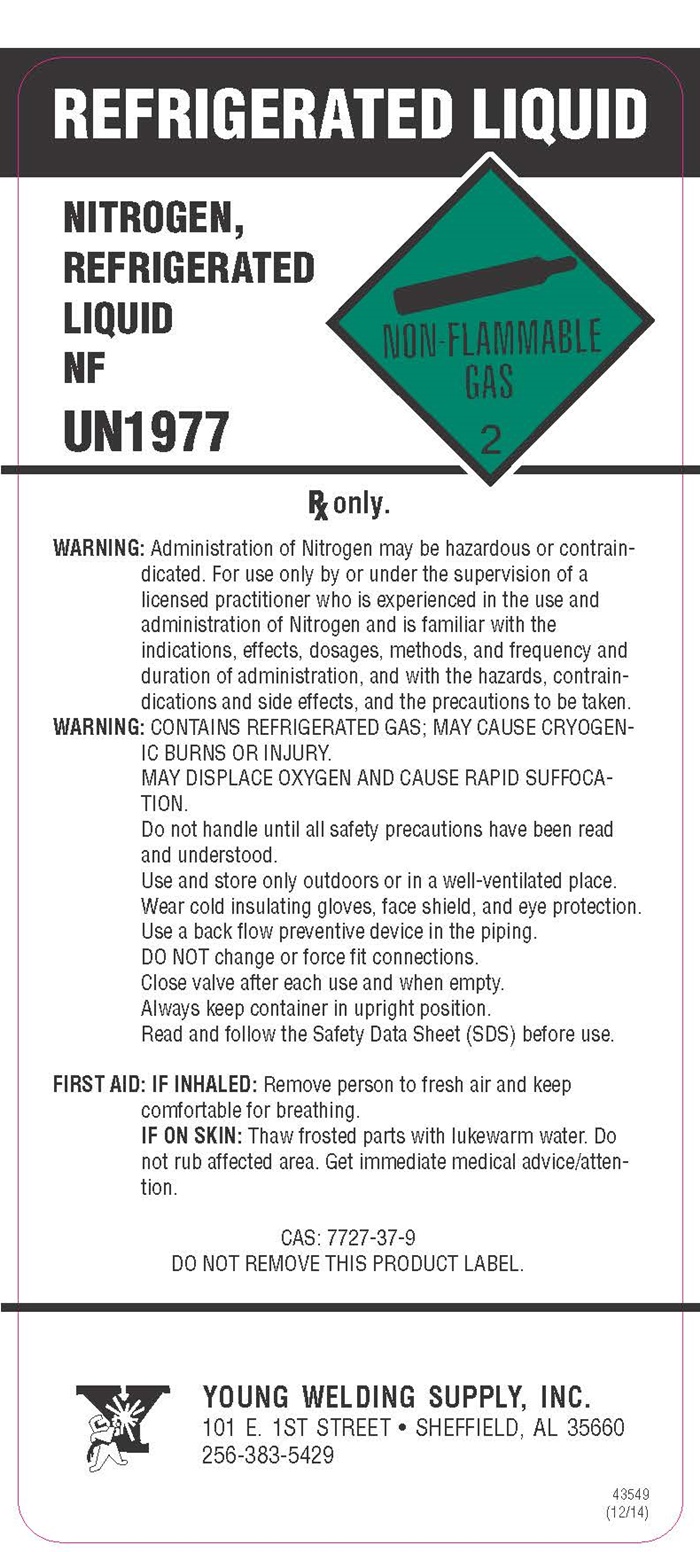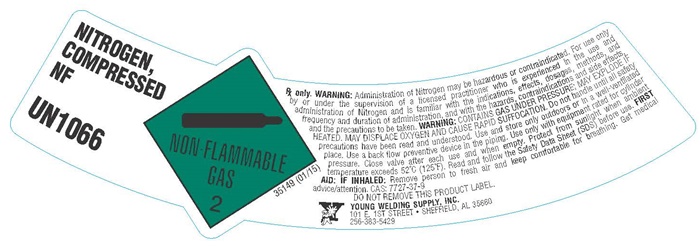 DRUG LABEL: Nitrogen
NDC: 58311-4444 | Form: GAS
Manufacturer: Young Welding Supply, Inc
Category: prescription | Type: HUMAN PRESCRIPTION DRUG LABEL
Date: 20251126

ACTIVE INGREDIENTS: NITROGEN 99 L/100 L

Nitrogen

PACKAGE LABEL

NITROGEN COMPRESSED NF

UN 1066

NON-FLAMMABLE GAS 2

35149 (01/15)
Rx only. WARNING: Administration of Nitrogen may be hazardous or contraindicated. For use only by or under the supervision of a licensed practitioner who is experienced in theuse and administration of Nitrogen and is familiar with the indications, effects, dosages, methods, and frequency and duration of administration, and with the hazards, contraindications, and side effects, and the precautions to be taken. WARNING: CONTAINS GAS UNDER PRESSURE; MAY EXPLODE IF HEATED. MAY DISPLACE OXYGEN AND CAUSE RAPID SUFFICATION. Do not handle until all safety precautions have been read and understood. Use and store only outdoors or in a well-ventilated place. Use a back flow preventive device in the piping. Use only with equipment rated for cylinder pressure. Close valve after each use and when empty. Protect from sunlight when the ambient temperature exceeds 52°C (125°F). Read and follow the Safety Data Sheet (SDS) before use. FIRST AID: IF INHALED: Remove the person to frexh are and keep comfortable for breathing. Get medical advice/attention. CAS:7727-37-9

DO NOT REMOVE THIS PRODUCT LABEL

YOUNG WELDING SUPPLY, INC.

101 E. 1ST STREET • SHEFFIELD, AL 35660

256-383-5429

PACKAGE LABEL

REFRIGERATED LIQUID

NITROGEN REFRIGERATED LIQUID NF

UN1977

NON-FLAMMABLE GAS-2

WARNING: Administration of Nitrogen may be hazardous or contraindicated. For use only by or under the supervision of a licensed practitioner who is experienced in theuse and administration of Nitrogen and is familiar with the indications, effects, dosages, methods, and frequency and duration of administration, and with the hazards, contraindications, and side effects, and the precautions to be taken.

WARNING: CONTAINS REFRIGERATED GAS; MAY CAUSE CRYOGENIC BURNS OR INJURY.

MAY DISPLACE OXYGEN AND CAUSE RAPID SUFFOCATION.

Do not handle until all safety precautions have been read and understood.

Use only outdoors or in a well-ventilated place.

Wear cold insulating gloves, face shield, and eye protection.

Use a back flow preventive device in the piping.

DO NOT change or force fit connections..

Close valve after each use and when emmpty.

Always keep container in upright position.

Read and follow the Safety Data Sheet (SDS) before use.

FIRST AID: IF INHALED: Remove person to fresh air and keep comfortable for breathing.

IF ON SKIN: Thaw frozen parts with lukewarm water. Do not rub affected area. Get immediate medical advice/attention.

CAS: 7727-37-9 DO NOT REMOVE THIS PRODUCT LABEL.

YOUNG WELDING SUPPLY, INC.

101 E. 1ST STREET • SHEFFIELD, AL 35660

256-383-5429